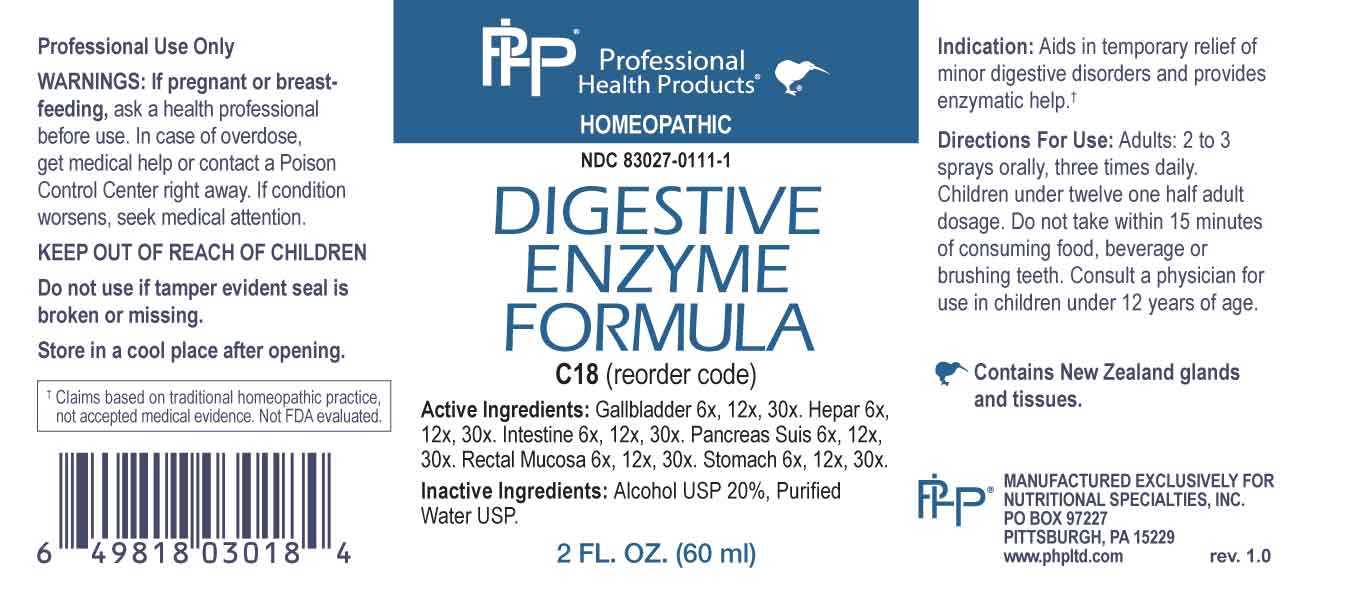 DRUG LABEL: Digestive Enzyme Formula
NDC: 83027-0111 | Form: SPRAY
Manufacturer: Nutritional Specialties, Inc.
Category: homeopathic | Type: HUMAN OTC DRUG LABEL
Date: 20231005

ACTIVE INGREDIENTS: BOS TAURUS GALLBLADDER 6 [hp_X]/1 mL; HEPARIN, BOVINE 6 [hp_X]/1 mL; PORK INTESTINE 6 [hp_X]/1 mL; SUS SCROFA PANCREAS 6 [hp_X]/1 mL; SUS SCROFA RECTAL MUCOSA 6 [hp_X]/1 mL; SUS SCROFA STOMACH 6 [hp_X]/1 mL
INACTIVE INGREDIENTS: WATER; ALCOHOL

DRUG FACTS:

ACTIVE INGREDIENTS:

Gallbladder 6X, 12X, 30X, Hepar 6X, 12X, 30X, Intestine 6X, 12X, 30X, Pancreas Suis 6X, 12X, 30X, Rectal Mucosa 6X, 12X, 30X, Stomach 6X, 12X, 30X.

PURPOSE:

Aids in temporary relief of minor digestive disorders and provides enzymatic help.†

†Claims based on traditional homeopathic practice, not accepted medical evidence. Not FDA evaluated.

WARNINGS:

Professional Use Only

If pregnant or breast-feeding, ask a health professional before use.

In case of overdose, get medical help or contact a Poison Control Center right away.

If condition worsens, seek medical attention.

KEEP OUT OF REACH OF CHILDREN

Do not use if tamper evident seal is broken or missing.

Store in a cool place after opening

KEEP OUT OF REACH OF CHILDREN:

In case of overdose, get medical help or contact a Poison Control Center right away.

DIRECTIONS:

Adults: 2 to 3 sprays orally, three times daily. Children under twelve one half adult dosage. Do not take within 15 minutes of consuming food, beverage or brushing teeth. Consult a physician for use in children under 12 years of age.

INDICATIONS:

Aids in temporary relief of minor digestive disorders and provides enzymatic help.†

†Claims based on traditional homeopathic practice, not accepted medical evidence. Not FDA evaluated.

INACTIVE INGREDIENTS:

Alcohol USP 20%, Purified Water USP.

QUESTIONS:

MANUFACTURED EXCLUSIVELY FOR

NUTRITIONAL SPECIALTIES, INC.

PO BOX 97227

PITTSBURG, PA 15229

www.phpltd.com

PACKAGE LABEL.PRINCIPAL DISPLAY PANEL

Professional

Health Products

HOMEOPATHIC

NDC 83027-0111-1

DIGESTIVE

ENZYME

FORMULA

2 FL. OZ (60 ml)